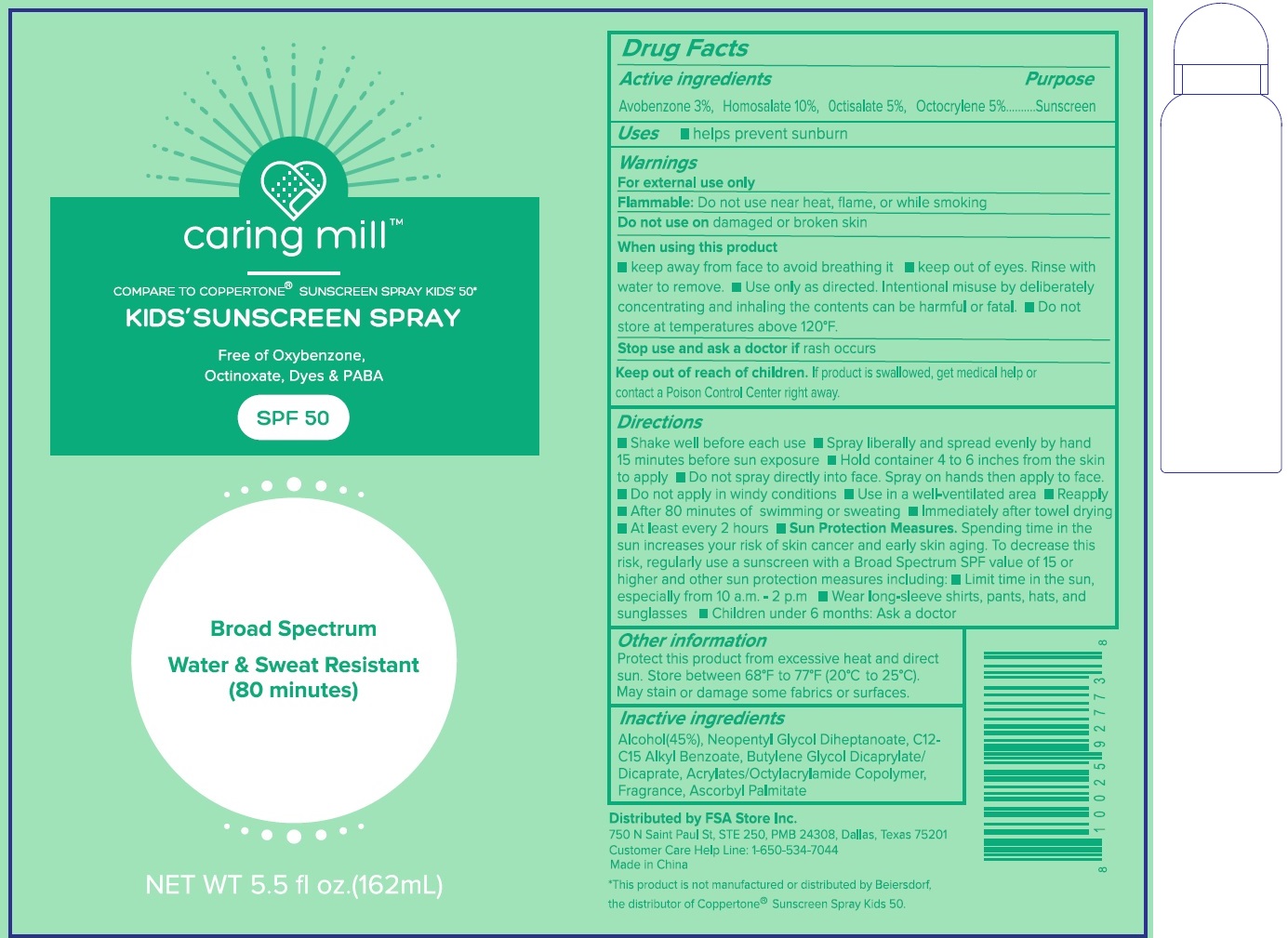 DRUG LABEL: Caring mill Kids Sunscreen SPF 50
NDC: 81522-954 | Form: LIQUID
Manufacturer: FSA Store Inc.
Category: otc | Type: HUMAN OTC DRUG LABEL
Date: 20240112

ACTIVE INGREDIENTS: AVOBENZONE 30 mg/1 mL; HOMOSALATE 100 mg/1 mL; OCTISALATE 50 mg/1 mL; OCTOCRYLENE 50 mg/1 mL
INACTIVE INGREDIENTS: BUTYLENE GLYCOL DICAPRYLATE/DICAPRATE; ASCORBYL PALMITATE; ALCOHOL; NEOPENTYL GLYCOL DIHEPTANOATE; ALKYL (C12-15) BENZOATE

Caring mill Kid’s Sunscreen Spray SPF 50

Active ingredients

Avobenzone 3%

Homosalate 10%

Octisalate 5%

Octocrylene 5%

Purpose

Sunscreen

Uses

- helps prevent sunburn

Warnings

For external use only

Flammable:Do not use near heat, flame, or while smoking

Do not use on

damaged or broken skin

when using this product

- keep away from face to avoid breathing it
- keep out of eyes. Rinse with water to remove.
- Use only as directed. Intentional misuse by deliberately concentrating and inhaling the contents can be harmful or fatal.
- Do not store at temperatures above 120°F

Stop use and ask a doctor if

rash occurs

Keep out of reach of children.

If product is swallowed, get medical help or contact a Poison Control Center right away.

Directions

- Shake well before each use
- Spray liberally and spread evenly by hand 15 minutes before sun exposure
- Hold container 4 to 6 inches from the skin to apply
- Do not spray directly into face. Spray on hands then apply to face.
- Do not apply in windy conditions
- Use in a well-ventilated area
- Reapply
- After 80 minutes of swimming or sweating
- Immediateky after towel drying
- At least every 2 hours
- Sun Protection Measures.Spending time in the sun increases your risk of skin cancer and early skin aging. To decrease this risk, regularly use a sunscreen with a Broad Spectrum SPF value of 15 or higher and other sun protection measures including:
- limit time in the sun, especially from 10 a.m.- 2 p.m
- Wear long-sleeve shirts, pants, hats, and sunglasses
- Children under 6 months: Ask a doctor

Other information

Protect this product from excessive heat and direct sun. Store between 68°F to 77°F (20°C to 25°C). May stain or damage some fabrics or surfaces.

Inactive ingredients

Alcohol(45%), Neopentyl Glycol Diheptanoate, C12-C15 Alkyl Benzoate, Butylene Glycol Dicaprylate/Dicaprate, Acrylates/Octylacrylamide Copolymer, Fragrance, Ascorbyl Palmitate